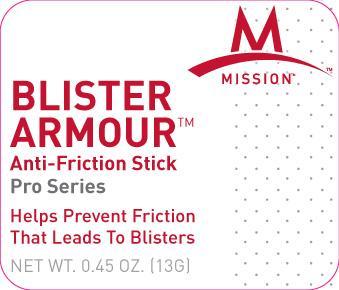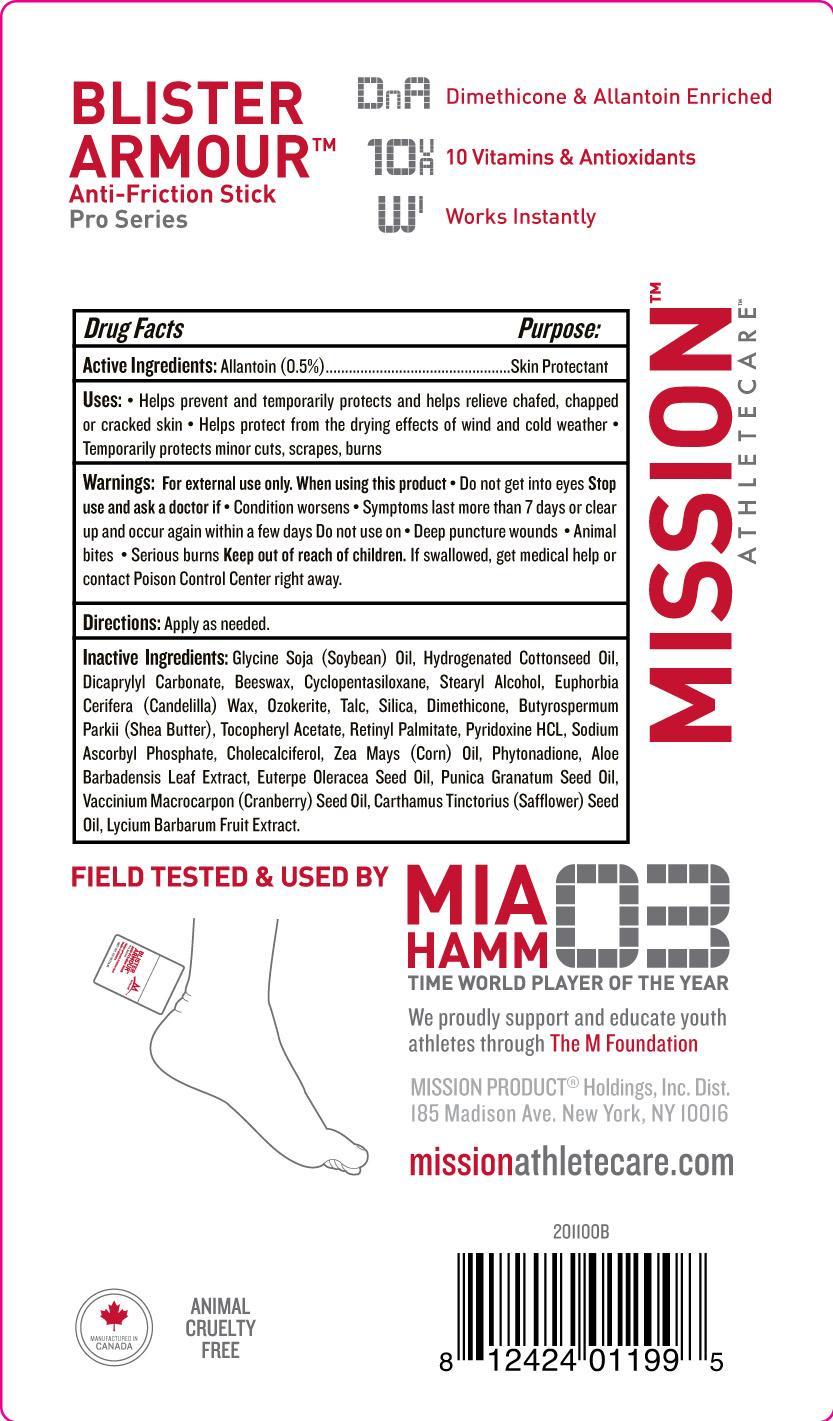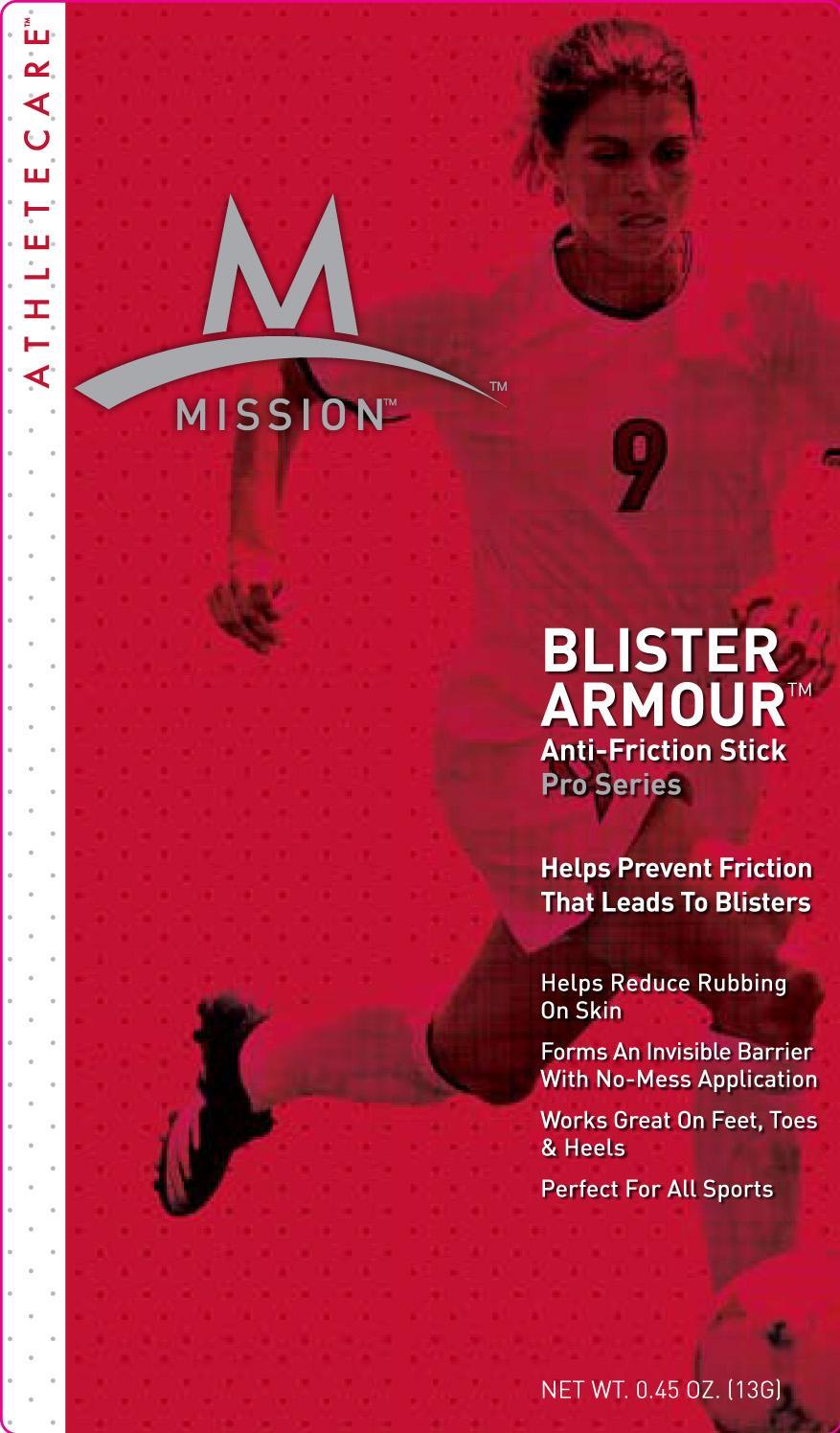 DRUG LABEL: Blister Armour Anti-Friction
NDC: 76347-126 | Form: STICK
Manufacturer: Mission Product Holdings
Category: otc | Type: HUMAN OTC DRUG LABEL
Date: 20130212

ACTIVE INGREDIENTS: ALLANTOIN 0.5 g/100 g
INACTIVE INGREDIENTS: HYDROGENATED COTTONSEED OIL; DICAPRYLYL CARBONATE; CYCLOMETHICONE 5; STEARYL ALCOHOL; CANDELILLA WAX; CERESIN; TALC; SILICON DIOXIDE; DIMETHICONE; SHEA BUTTER; VITAMIN A PALMITATE; PYRIDOXINE HYDROCHLORIDE; SODIUM ASCORBYL PHOSPHATE; CHOLECALCIFEROL; ALOE VERA LEAF; POMEGRANATE SEED OIL; CRANBERRY SEED OIL; SAFFLOWER OIL; LYCIUM BARBARUM FRUIT

Blister Armour Anti-Friction Stick

Active Ingredients Purpose

Allantoin Skin Protectant

Uses

Helps prevent and temporarily protects and helps relieve chafed, chapped, or cracked skin

Helps protect from the drying effects of wind and cold weather

Temporarily protects minor cuts, scrapes, burns

Keep out of reach of children

Stop use and ask a doctor if

Condition worsens

Symptoms last more than 7 days or clear up and occur again within a few days

Warnings: For external use only.

When using this product

- Do not get into eyes

Do not use on
- Deep Puncture wounds
- Animal bites
- Serious burns
If swallowed, get medical help or contact poison control right away.

DOSAGE AND ADMINISTRATION

Directions: Apply as needed

Inactive Ingredients

Glycine Soja (Soybean) Oil, Hydrogenated Cottonseed Oil, Dicaprylyl Carbonate, Beeswax, Cyclopentasiloxane, Stearyl Alcohol, Euphorbia Cerfiera (Candelila) Wax, Ozokerite, Talc, Silica, Dimethicone, Butyrospermum Parkii (Shea Butter), Tocopheryl Acetate, Retinyl Palmitate, Pyridoxine HCL, Sodium Ascorbyl Phosphate, Cholcalciferol, Zea Mays (Corn) Oil, Phytonadione, Aloe Barbadensis Leaf Extract, Euterpe Oleracea Seed Oil, Punica Granatum Seed Oil, Vaccinum Macrocarpon (Cranberry) Seed Oil, Carthamus Tinctorius (Safflower) Seed Oil, Lycium Barbarum Fruit Extract.

PACKAGE LABEL

Mission

Blister Armour (TM)

Anti-Friction Stick

Pro Series

Helps Prevent Friction that Leads to Blisters
Net. Wt. 0.45 OZ. (13G)